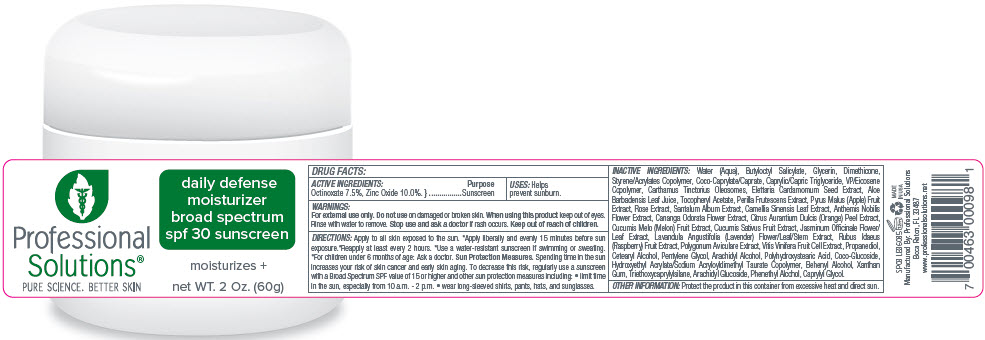 DRUG LABEL: Professional Solutions - Botanical Day Cream Broad Spectrum SPF 30 Sunscreen
NDC: 66163-0300 | Form: CREAM
Manufacturer: Cosmetic Solutions LLC
Category: otc | Type: HUMAN OTC DRUG LABEL
Date: 20230119

ACTIVE INGREDIENTS: Octinoxate 7.5 g/100 g; Zinc Oxide 10 g/100 g
INACTIVE INGREDIENTS: Water; Butyloctyl Salicylate; Glycerin; Dimethicone; Styrene/Acrylamide Copolymer (500000 MW); Cocoyl Caprylocaprate; Medium-Chain Triglycerides; Carthamus Tinctorius Seed Oleosomes; Cardamom; Aloe Vera Leaf; .Alpha.-Tocopherol Acetate; Perilla Frutescens Seed; Apple; Santalum Album Seed; Green Tea Leaf; Chamaemelum Nobile Flower; Cananga Odorata Flower; Orange Peel; Muskmelon; Jasminum Officinale Flower; Lavandula Angustifolia Subsp. Angustifolia Flowering Top; Raspberry; Polygonum Aviculare Top; Propanediol; Cetostearyl Alcohol; Pentylene Glycol; Arachidyl Alcohol; Coco Glucoside; Hydroxyethyl Acrylate/Sodium Acryloyldimethyl Taurate Copolymer (100000 MPA.S AT 1.5%); Docosanol; Xanthan Gum; Triethoxycaprylylsilane; Arachidyl Glucoside; Phenylethyl Alcohol; Caprylyl Glycol

Professional Solutions® - Botanical Day Cream Broad Spectrum SPF 30 Sunscreen

DRUG FACTS:

ACTIVE INGREDIENTS

Octinoxate 7.5%, Zinc Oxide 10.0%.

Purpose

Sunscreen

USES

Helps prevent sunburn.

WARNINGS

For external use only. Do not use on damaged or broken skin. When using this product keep out of eyes. Rinse with water to remove. Stop use and ask a doctor if rash occurs.

Keep out of reach of children.

DIRECTIONS

Apply to all skin exposed to the sun. *Apply liberally and evenly 15 minutes before sun exposure.*Reapply at least every 2 hours. *Use a water-resistant sunscreen if swimming or sweating. *For children under 6 months of age: Ask a doctor. Sun Protection Measures. Spending time in the sun increases your risk of skin cancer and early skin aging. To decrease this risk, regularly use a sunscreen with a Broad Spectrum SPF value of 15 or higher and other sun protection measures including:

- limit time in the sun, especially from 10 a.m. - 2 p.m.
- wear long-sleeved shirts, pants, hats, and sunglasses.

INACTIVE INGREDIENTS

Water (Aqua), Butyloctyl Salicylate, Glycerin, Dimethicone, Styrene/Acrylates Copolymer, Coco-Caprylate/Caprate, Caprylic/Capric Triglyceride, VP/Eicosene Copolymer, Carthamus Tinctorius Oleosomes, Elettaria Cardamomum Seed Extract, Aloe Barbadensis Leaf Juice, Tocopheryl Acetate, Perilla Frutescens Extract, Pyrus Malus (Apple) Fruit Extract, Rose Extract, Santalum Album Extract, Camellia Sinensis Leaf Extract, Anthemis Nobilis Flower Extract, Cananga Odorata Flower Extract, Citrus Aurantium Dulcis (Orange) Peel Extract, Cucumis Melo (Melon) Fruit Extract, Cucumis Sativus Fruit Extract, Jasminum Officinale Flower/Leaf Extract, Lavandula Angustifolia (Lavender) Flower/Leaf/Stem Extract, Rubus Idaeus (Raspberry) Fruit Extract, Polygonum Aviculare Extract, Vitis Vinifera Fruit Cell Extract, Propanediol, Cetearyl Alcohol, Pentylene Glycol, Arachidyl Alcohol, Polyhydroxystearic Acid, Coco-Glucoside, Hydroxyethyl Acrylate/Sodium Acryloyldimethyl Taurate Copolymer, Behenyl Alcohol, Xanthan Gum, Triethoxycaprylylsilane, Arachidyl Glucoside, Phenethyl Alcohol, Caprylyl Glycol.

OTHER INFORMATION

Protect the product in this container from excessive heat and direct sun.

Manufactured By: Professional Solutions
Boca Raton, FL 33487

PRINCIPAL DISPLAY PANEL - 60 g Jar Label

Professional
Solutions®

PURE SCIENCE. BETTER SKIN

daily defense
moisturizer
broad spectrum
spf 30 sunscreen

moisturizes +

net WT. 2 Oz. (60g)